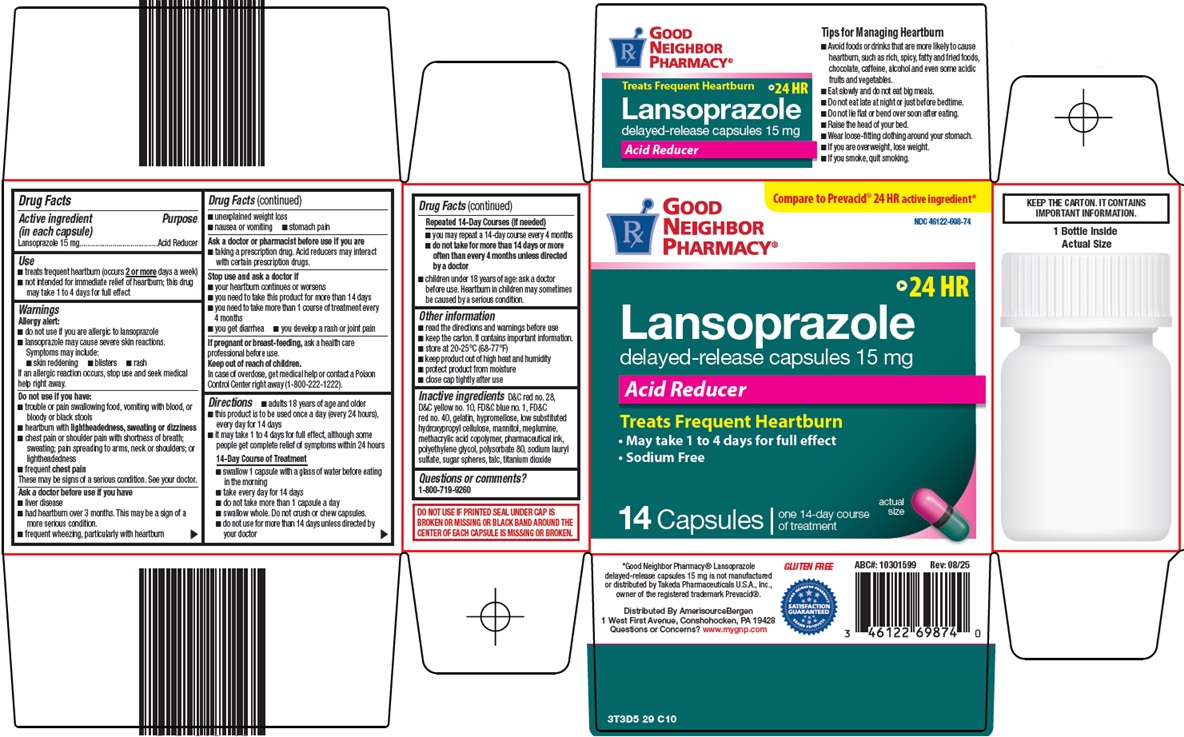 DRUG LABEL: good neighbor pharmacy lansoprazole
NDC: 46122-698 | Form: CAPSULE, DELAYED RELEASE
Manufacturer: Amerisource Bergen
Category: otc | Type: HUMAN OTC DRUG LABEL
Date: 20251201

ACTIVE INGREDIENTS: LANSOPRAZOLE 15 mg/1 1
INACTIVE INGREDIENTS: D&C RED NO. 28; D&C YELLOW NO. 10; FD&C BLUE NO. 1; FD&C RED NO. 40; GELATIN, UNSPECIFIED; HYPROMELLOSE, UNSPECIFIED; LOW-SUBSTITUTED HYDROXYPROPYL CELLULOSE, UNSPECIFIED; MANNITOL; MEGLUMINE; METHACRYLIC ACID AND ETHYL ACRYLATE COPOLYMER; POLYETHYLENE GLYCOL, UNSPECIFIED; POLYSORBATE 80; SODIUM LAURYL SULFATE; TALC; TITANIUM DIOXIDE

Amerisource Bergen Lansoprazole Drug Facts

Active ingredient (in each capsule)

Lansoprazole 15 mg

Purpose

Acid Reducer

Use

- treats frequent heartburn (occurs 2 or more days a week)
- not intended for immediate relief of heartburn; this drug may take 1 to 4 days for full effect

Warnings

Allergy alert:

- do not use if you are allergic to lansoprazole
- lansoprazole may cause severe skin reactions.
Symptoms may include:
  - skin reddening
  - blisters
  - rash

If an allergic reaction occurs, stop use and seek medical help right away.

Do not use if you have:

- trouble or pain swallowing food, vomiting with blood, or bloody or black stools.
- heartburn with lightheadedness, sweating or dizziness
- chest pain or shoulder pain with shortness of breath; sweating; pain spreading to arms, neck or shoulders; or lightheadedness
- frequent chest pain
  These may be signs of a serious condition. See your doctor.

Ask a doctor before use if you have

- liver disease
- had heartburn over 3 months. This may be a sign of a more serious condition.
- frequent wheezing, particularly with heartburn
- unexplained weight loss
- nausea or vomiting
- stomach pain

Ask a doctor or pharmacist before use if you are

- taking a prescription drug. Acid reducers may interact with certain prescription drugs.

Stop use and ask a doctor if

- your heartburn continues or worsens
- you need to take this product for more than 14 days
- you need to take more than 1 course of treatment every 4 months
- you get diarrhea
- you develop a rash or joint pain

If pregnant or breast-feeding,

ask a health professional before use.

Keep out of reach of children.

In case of overdose, get medical help or contact a Poison Control Center right away (1-800-222-1222).

Directions

- adults 18 years of age and older
- this product is to be used once a day (every 24 hours), every day for 14 days
- it may take 1 to 4 days for full effect, although some people get complete relief of symptoms within 24 hours

14-Day Course of Treatment

- swallow 1 capsule with a glass of water before eating in the morning
- take every day for 14 days
- do not take more than 1 capsule a day
- swallow whole. Do not crush or chew capsules.
- do not use for more than 14 days unless directed by your doctor

Repeated 14-Day Courses (if needed)

- you may repeat a 14-day course every 4 months
- do not take for more than 14 days or more often than every 4 months unless directed by a doctor
- children under 18 years of age: ask a doctor before use. Heartburn in children may sometimes be caused by a serious condition.

Other information

- read the directions and warnings before use
- keep the carton. It contains important information.
- store at 20-25°C (68-77°F)
- keep product out of high heat and humidity
- protect product from moisture
- close cap tightly after use

Inactive ingredients

D&C red no. 28, D&C yellow no. 10, FD&C blue no. 1, FD&C red no. 40, gelatin, hypromellose, low substituted hydroxypropyl cellulose, mannitol, meglumine, methacrylic acid copolymer, pharmaceutical ink, polyethylene glycol, polysorbate 80, sodium lauryl sulfate, sugar spheres, talc, titanium dioxide

Questions or comments?

1-800-719-9260

Package/Label Principal Display Panel

Compare to Prevacid® 24 HR active ingredient

GOOD NEIGHBOR PHARMACY®

24 HR

Lansoprazole delayed-release capsules 15 mg

Acid Reducer

Treats Frequent Heartburn

• May take 1 to 4 days for full effect

• Sodium Free

14 Capsules

one 14-day course of treatment

actual size